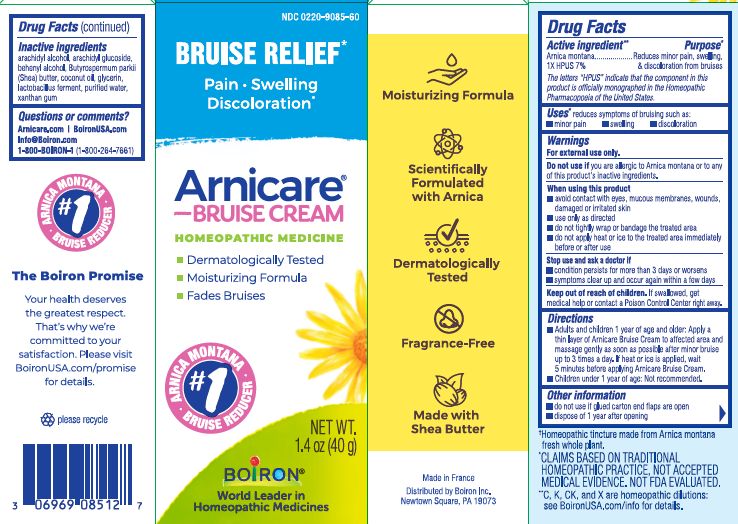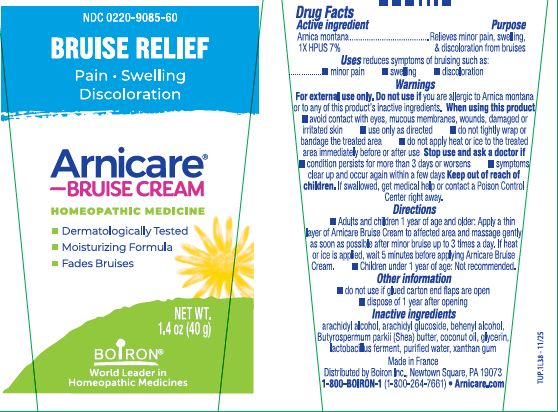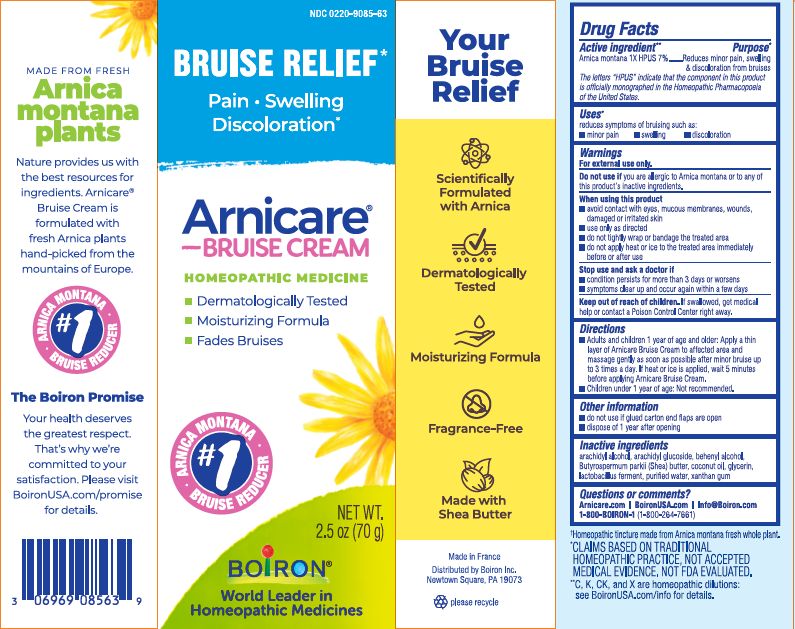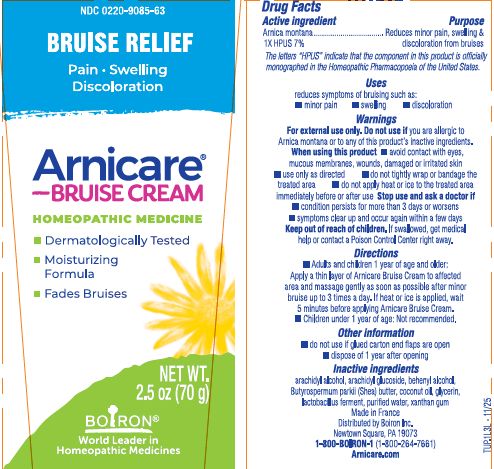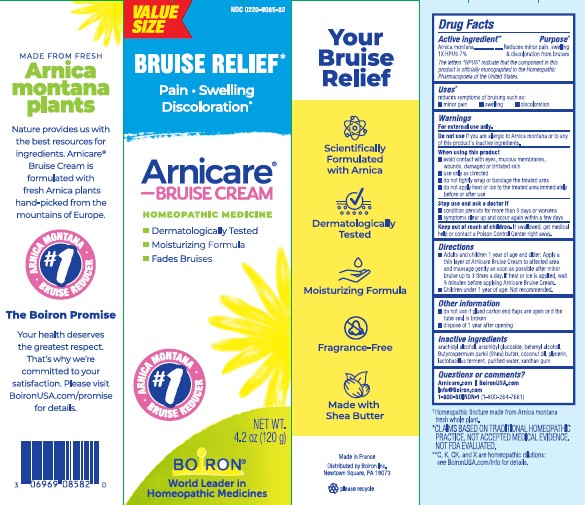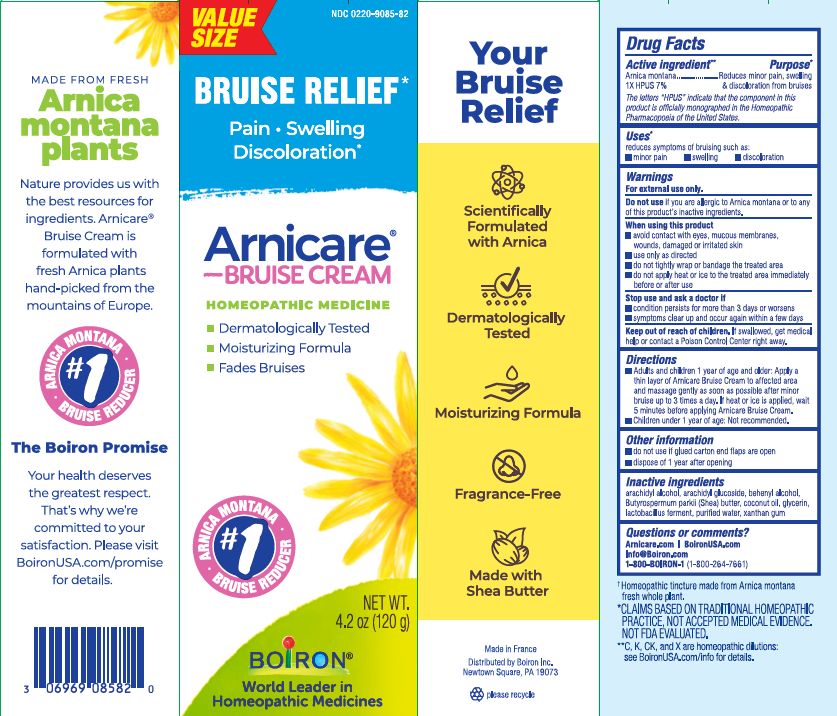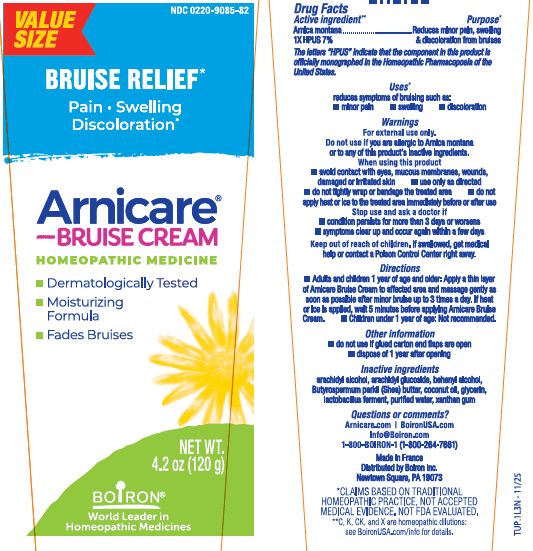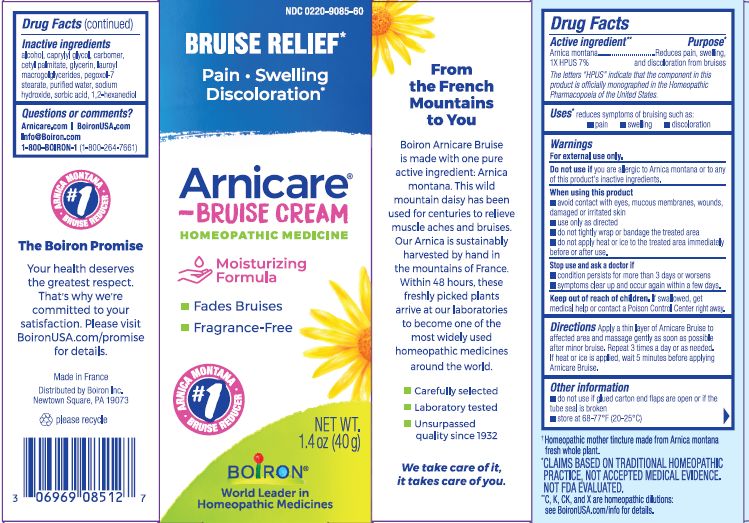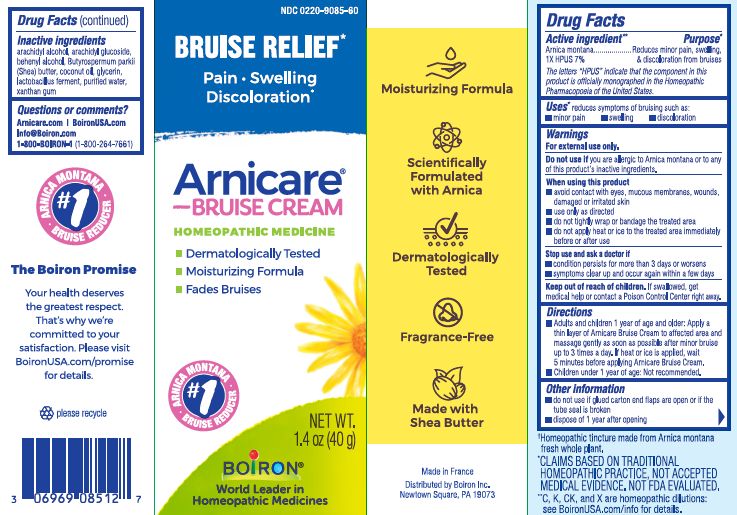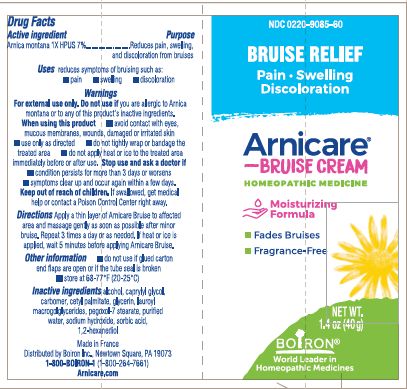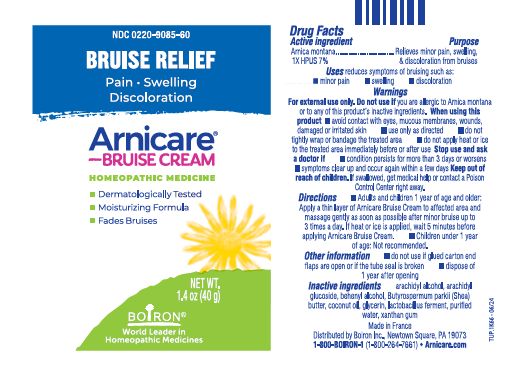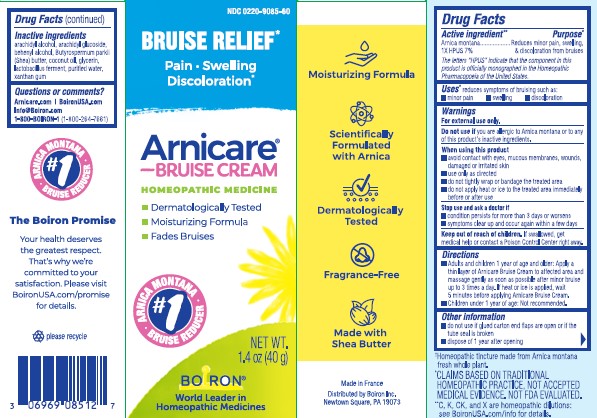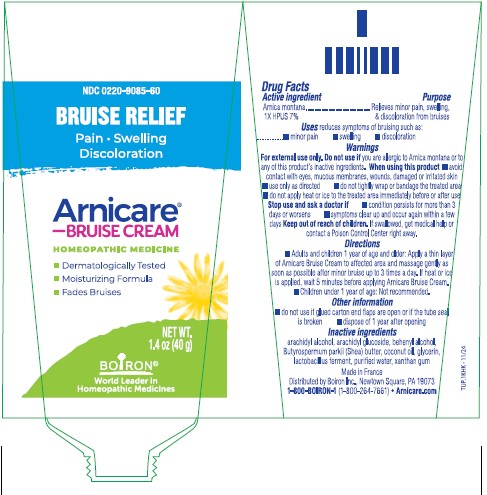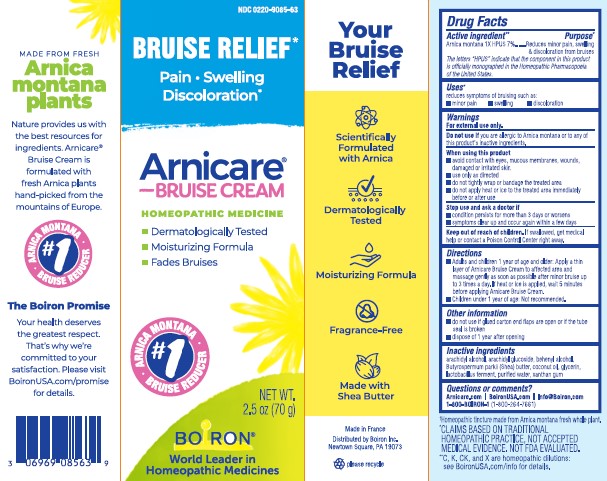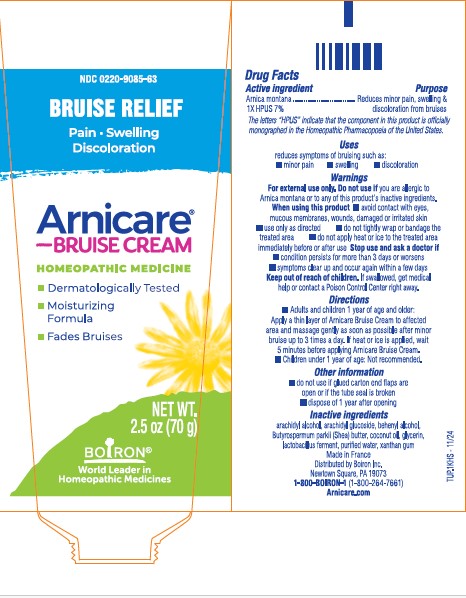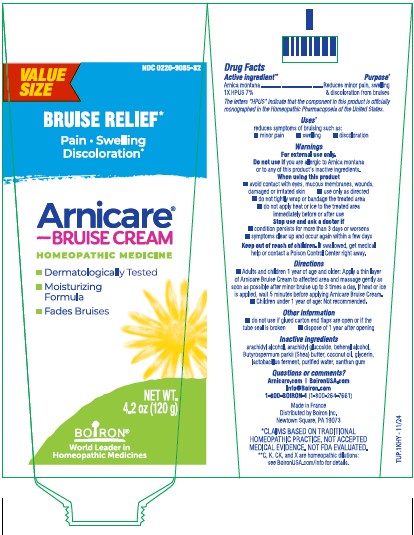 DRUG LABEL: Arnicare Bruise
NDC: 0220-9085 | Form: CREAM
Manufacturer: Boiron
Category: homeopathic | Type: HUMAN OTC DRUG LABEL
Date: 20251211

ACTIVE INGREDIENTS: ARNICA MONTANA 1 [hp_X]/1 [hp_X]
INACTIVE INGREDIENTS: DOCOSANOL; LIMOSILACTOBACILLUS FERMENTUM; WATER; XANTHAN GUM; COCONUT OIL; ARACHIDYL ALCOHOL; BUTYROSPERMUM PARKII (SHEA) BUTTER UNSAPONIFIABLES; ARACHIDYL GLUCOSIDE; GLYCERIN

Arnicare Bruise Cream

Active ingredient**

Arnica montana 1X HPUS 7%

The letters "HPUS" indicate that the component in this product are officially monographed in the Homeopathic Pharmacopoeia of the United States.

Purpose*

Reduces minor pain, swelling, & discoloration from bruises

Uses*

reduces symptoms of bruising such as:

- minor pain
- swelling
- discoloration

WARNINGS

For external use only.

Do not use if you are allergic to Arnica montana or to any of this product's inactive ingredients.

When using this product

- avoid contact with eyes, mucous membranes, wounds, damaged or irritated skin
- use only as directed
- do not tightly wrap or bandage the treated area
- do not apply heat or ice to the treated area immediately before or after use

Stop use and ask a doctor if

- condition persists for more than 3 days or worsens
- symptoms clear up and occur again within a few days

Keep out of reach of children. If swallowed, get medical help or contact a Poison Control Center right away.

Directions

- Adults and children 1 year of age and older: Apply a thin layer of Arnicare Bruise Cream to affected area and massage gently as soon as possible after minor bruise up to 3 times a day. If heat or ice is applied, wait 5 minutes before applying Arnicare Bruise Cream.
- Children under 1 year of age: Not recommended.

Other information

- do not use if glued carton end flaps are open
- dispose of 1 year after opening

1.4 oz (40 g)

2.5 oz (70 g)

4.2 oz (120 g)

Bruise Relief*

Pain Swelling Discoloration*

ɨ Homeopathic mother tincture made from Arnica montana fresh whole plant.

*CLAIMS BASED ON TRADITIONAL HOMEOPATHIC PRACTICE, NOT ACCEPTED MEDICAL EVIDENCE. NOT FDA EVALUATED.

**C,K,CK, and X are homeopathic dilutions: see BoironUSA.com/info for details.

INACTIVE INGREDIENT

arachidyl alcohol, arachidyl glucoside, behenyl alcohol, Butyrospermum parkii (Shea) butter, coconut oil, glycerin, lactobacillus ferment, purified water, xanthan gum

Questions or comments?

Arnicare.com | BoironUSA.com

Info@Boiron.com

1-800-BOIRON-1 (1-800-264-7661)